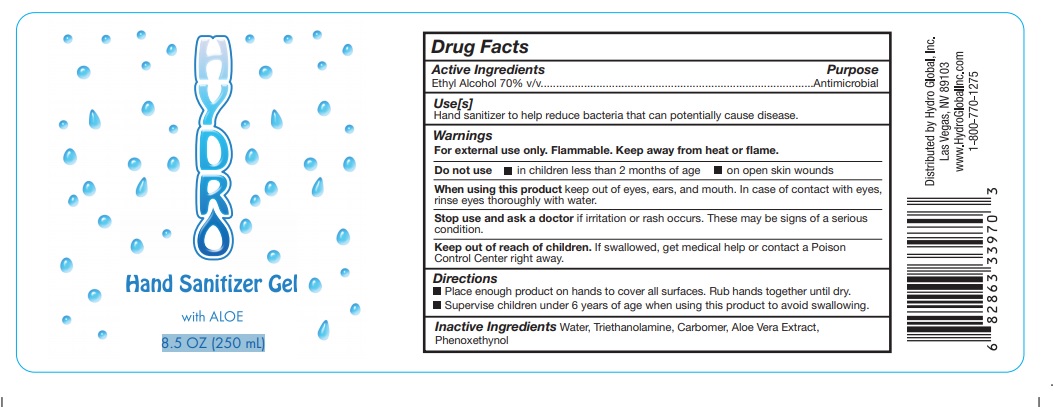 DRUG LABEL: Hydro
NDC: 77994-100 | Form: GEL
Manufacturer: HYDRO GLOBAL INC
Category: otc | Type: HUMAN OTC DRUG LABEL
Date: 20200714

ACTIVE INGREDIENTS: ALCOHOL 0.7 mL/1 mL
INACTIVE INGREDIENTS: PHENOXYETHANOL 0.0003 mL/1 mL; ALOE VERA LEAF 0.001 mL/1 mL; CARBOMER HOMOPOLYMER, UNSPECIFIED TYPE 0.002 mL/1 mL; WATER 0.4 mL/1 mL; TROLAMINE 0.0025 mCi/1 mL

Active Ingredient(s)

Ethyl Alcohol 70% v/v ......................Antimicrobial

Purpose

Antimicrobial, Hand Sanitizer

Use

Hand Sanitizer to help reduce bacteria that potentially can cause disease. For use when soap and water are not available.

Warnings

For external use only. Flammable. Keep away from heat or flame

Do not use

- in children less than 2 months of age
- on open skin wounds

When using this product keep out of eyes, ears, and mouth. In case of contact with eyes, rinse eyes thoroughly with water.
Stop use and ask a doctor if irritation or rash occurs. These may be signs of a serious condition.
Keep out of reach of children. If swallowed, get medical help or contact a Poison Control Center right away.

Stop use and ask a doctor if irritation or rash occurs. These may be signs of a serious condition.

Keep out of reach of children. If swallowed, get medical help or contact a Poison Control Center right away.

Directions

- Place enough product on hands to cover all surfaces. Rub hands together until dry.
- Supervise children under 6 years of age when using this product to avoid swallowing.

Other information

- Store between 15-30C (59-86F)

Inactive ingredients

Water, Triethanolamine, Carbomer, Aloe Vera Extract, Phenoxethynol

RECENT MAJOR CHANGES

na

Package Label - Principal Display Panel

HYDRO Hand Sanitizer Gel with Aloe

8.5 OZ (250 mL)